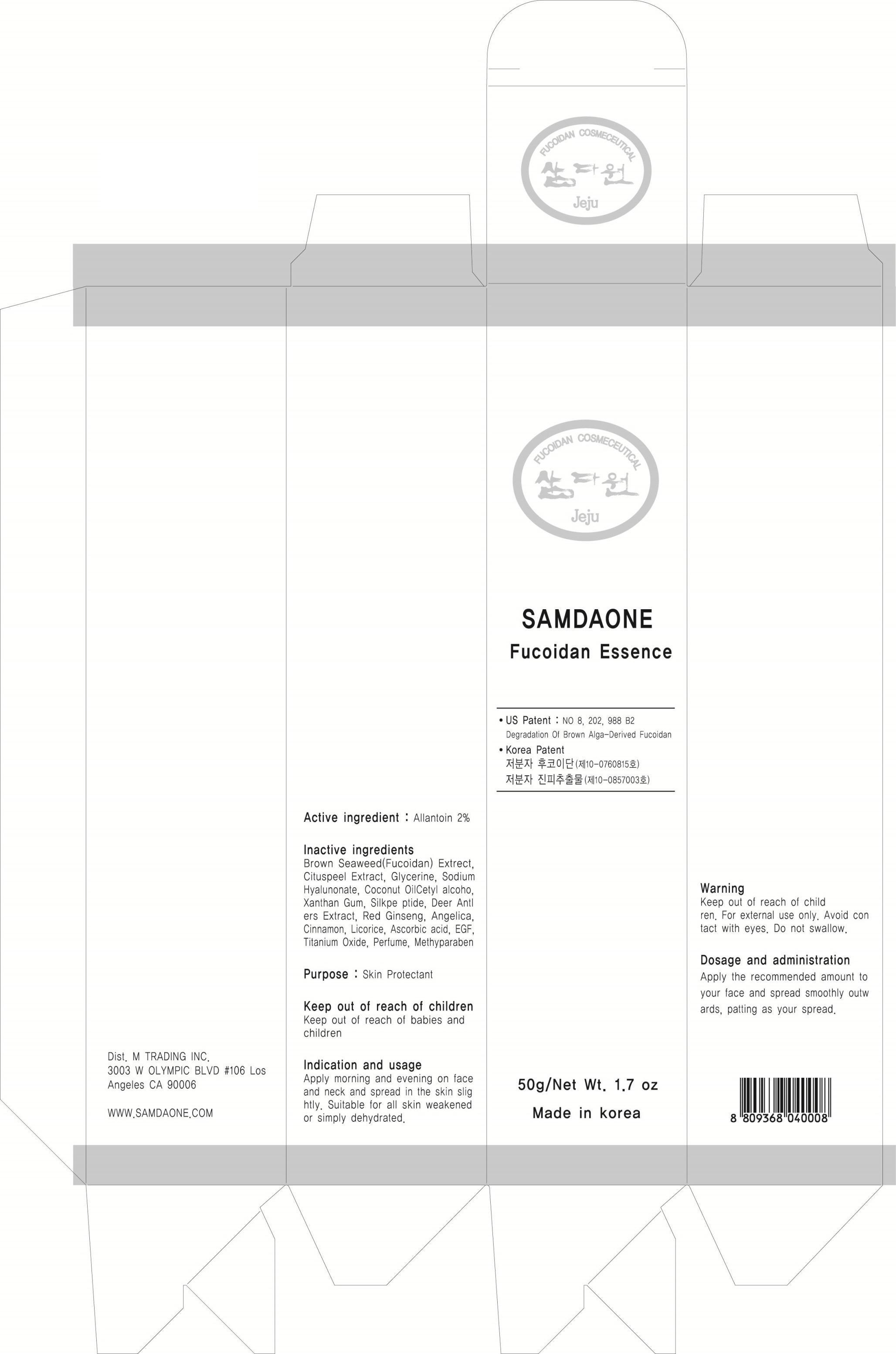 DRUG LABEL: FUCOIDAN ESSENCE
NDC: 58986-020 | Form: CREAM
Manufacturer: SAMDAONE
Category: otc | Type: HUMAN OTC DRUG LABEL
Date: 20130822

ACTIVE INGREDIENTS: Allantoin 1 g/50 g
INACTIVE INGREDIENTS: Xanthan Gum; METHYLPARABEN

ACTIVE INGREDIENT

Active ingredient: Allantoin 2%

INACTIVE INGREDIENT

Inactive ingredients:
Brown Seaweed(Fucoidan) Extrect, Cituspeel Extract, Deer Amtlers Extract, Red Ginseng, Angelica, Cinnamon, Licorice, Glycerin, Sodium Hyalunonate, Coconut Oil, Cetyl alcohol, Xanthan Gum, Silkpeptide, EGF, Ascorbic acid, Titanium Oxide, Perfume, Methylparaben

PURPOSE

Purpose: Skin protectant

WARNINGS

Warning:
Keep out of reach of children.
For external use only.
Avoid contact with eyes.
Do not swallow.

KEEP OUT OF REACH OF CHILDREN

Keep out of reach of babies and children.

INDICATIONS AND USAGE

Indication and usage:
Apply morning and evening on face and neck and spread in the skin slightly.
Suitable for all skin weakened or simply dehydrated.

DOSAGE AND ADMINISTRATION

Apply the recommended amount to your face and spread smoothly outwards, patting as your spread.